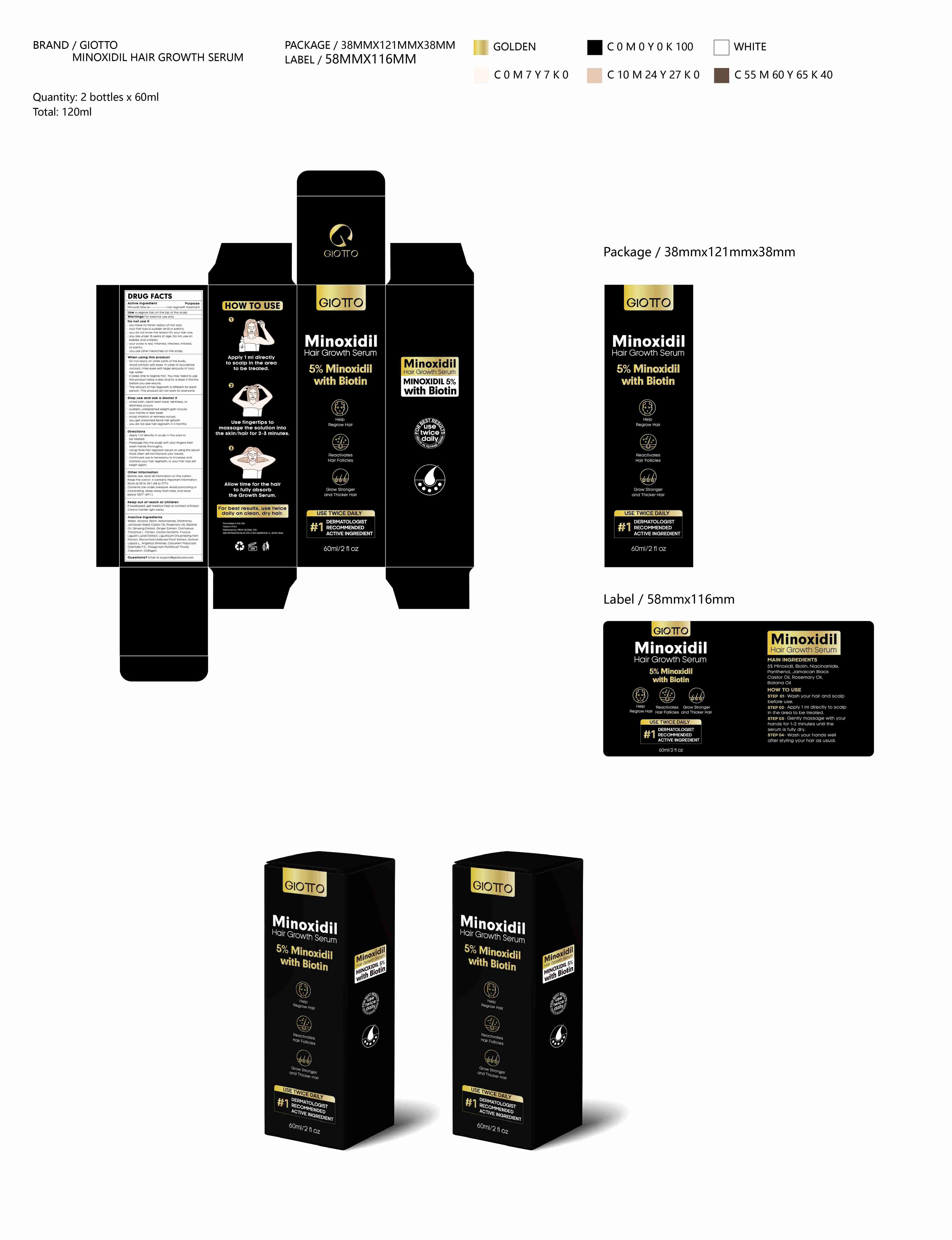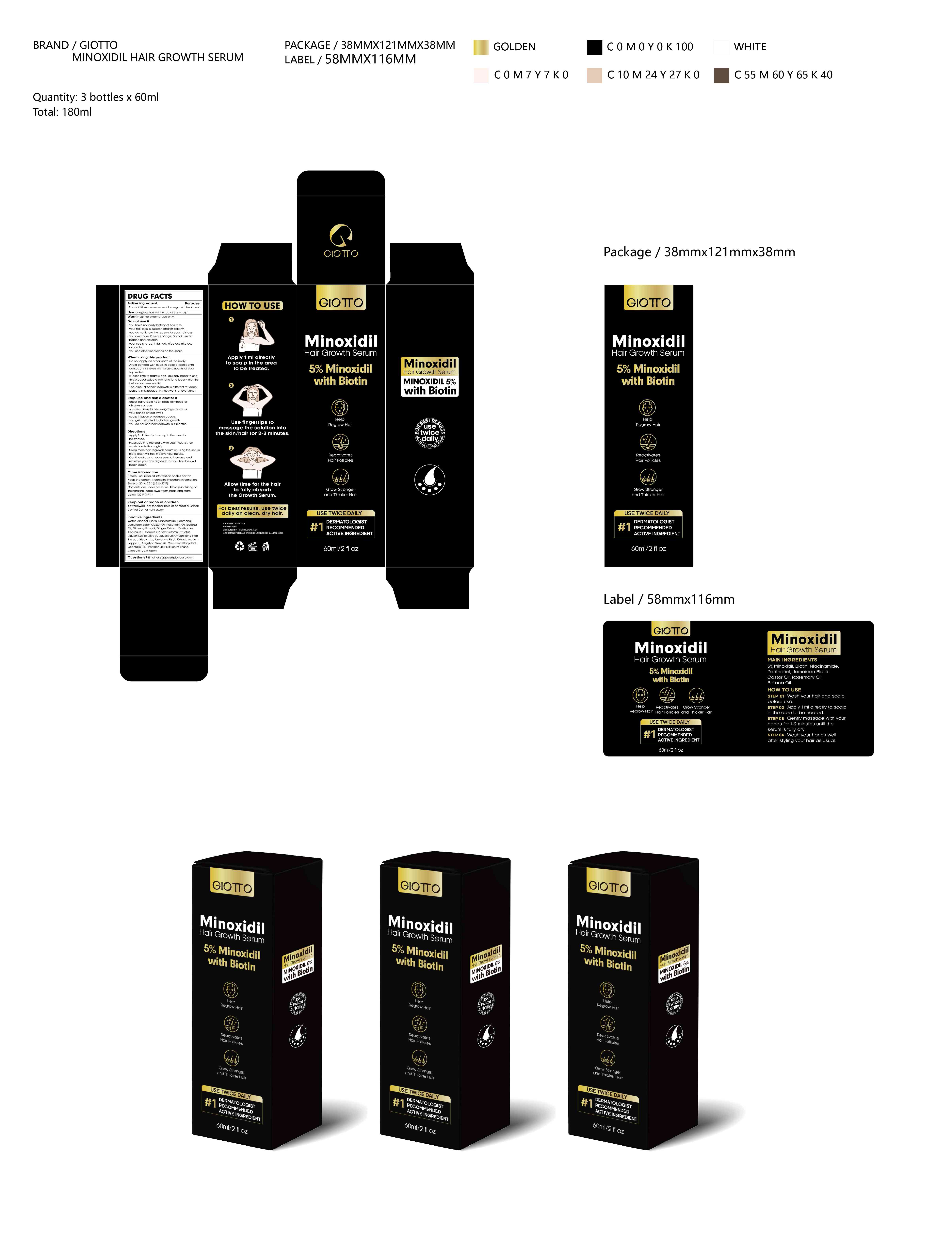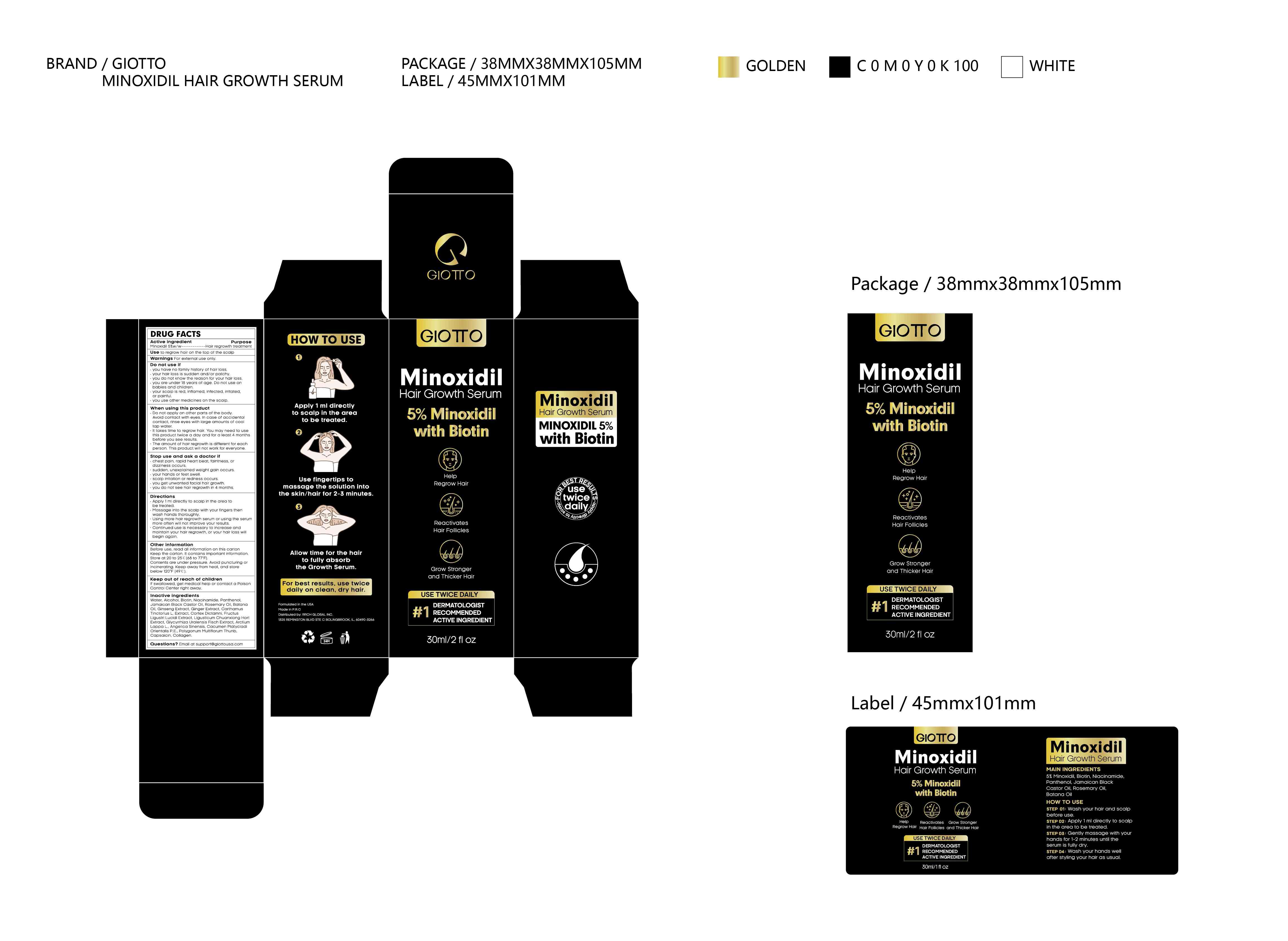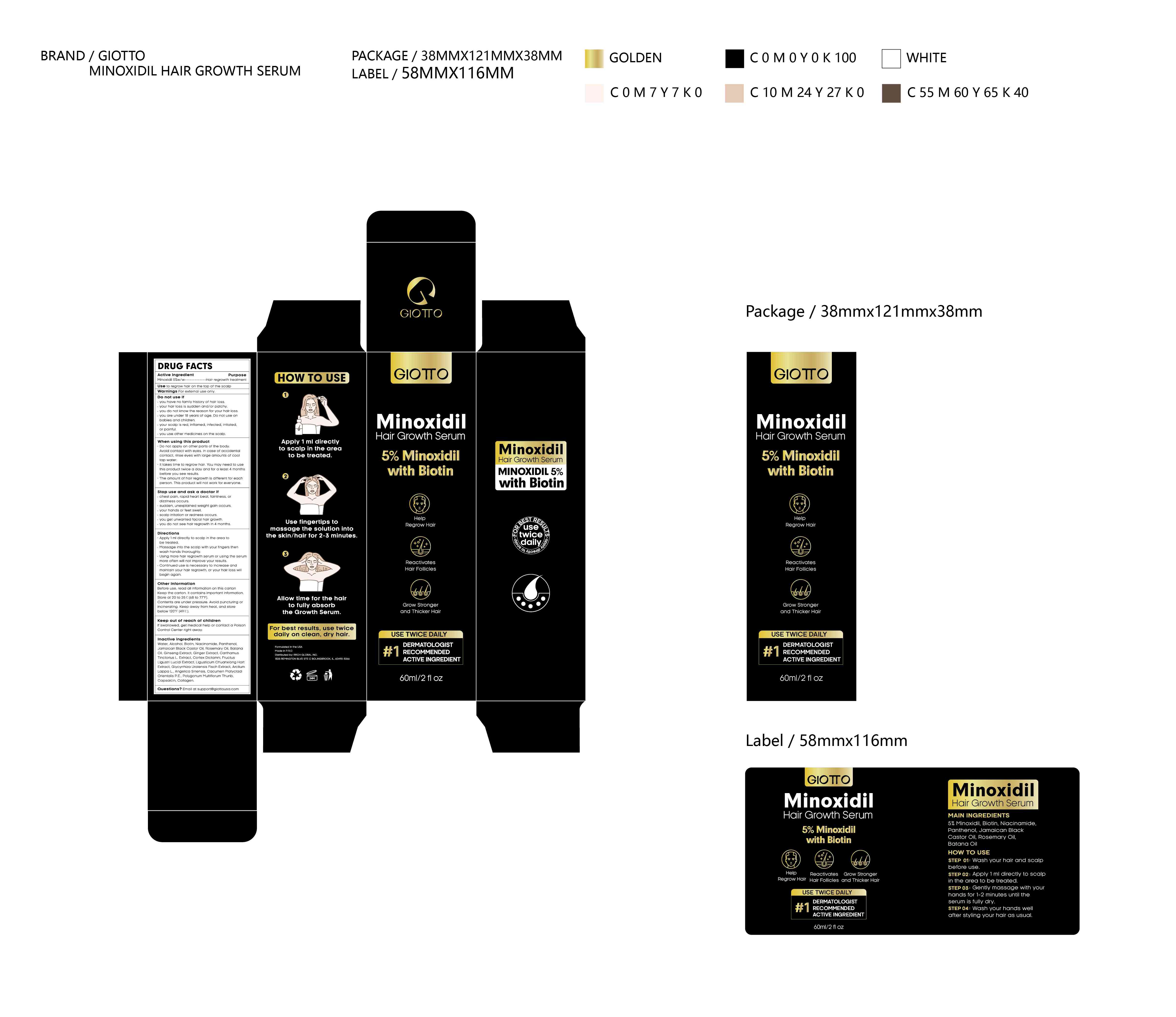 DRUG LABEL: GIOTTO Minoxidil Hair Growth Serum
NDC: 83910-001 | Form: LIQUID
Manufacturer: Xiamen Beishan Ecommerce Co.,LTD
Category: otc | Type: HUMAN OTC DRUG LABEL
Date: 20240103

ACTIVE INGREDIENTS: MINOXIDIL 5 g/100 mL
INACTIVE INGREDIENTS: ANGELICA SINENSIS ROOT OIL; PLATYCLADUS ORIENTALIS LEAF; ASIAN GINSENG; GLYCYRRHIZA URALENSIS WHOLE; PANTHENOL; CASTOR OIL; POLYGONATUM MULTIFLORUM ROOT; BIOTIN; DICTAMNUS DASYCARPUS ROOT BARK; LIGUSTRUM LUCIDUM FRUIT; LIGUSTICUM SINENSE SUBSP. CHUANXIONG ROOT; NIACINAMIDE; WATER; OENOCARPUS BATAUA SEED OIL; CAPSAICIN; CARTHAMUS TINCTORIUS WHOLE; ROSEMARY OIL

83910-001

Active Ingredient

Minoxidil 5%

Purpose

Hair regrowth treatment

Use

to regrow hair on the top of the scalp

Warnings

For external use only

Do not use

you have no family history of hair loss
your hair loss is sudden and/or patchy
you do not know the reason for your hair loss
you are under 18 years of age. Do not use on babies and children
your scalp is red, inflamed, infected, irritated, or painful
you use other medicines on the scalp

When Using

Do not apply on other parts of the body.
Avoid contact with eyes. In case of accidental contact, rinse eyes with large amounts of cool tap water.
lt takes time to regrow hair. You may need to use this product twice a day and for a least 4 months before you see results.
The amount of hair regrowth is different for each person. This product will not work for everyone.

Stop Use

Stop use and ask a doctor if
chest pain, rapid heart beat, faintness, ordizziness occurs
sudden, unexplained weight gain occurs.
your hands or feet swell
scalp irritation or redness occurs
you get unwanted facial hair growth
you do not see hair regrowth in 4 months

Ask Doctor

Stop use and ask a doctor if
chest pain, rapid heart beat, faintness, ordizziness occurs
sudden, unexplained weight gain occurs.
your hands or feet swell
scalp irritation or redness occurs
you get unwanted facial hair growth
you do not see hair regrowth in 4 months

Keep Oot Of Reach Of Children

Keep out of reach of children
If swallowed, get medical help or contact a Poison Control Center right away.

Directions

Apply 1 ml directly to scalp in the area to
be treated
Massage into the scalp with your fingers then wash hands thoroughly
Using more hair regrowth serum or using the serum more often will not improve your results
Continued use is necessary to increase andmaintain your hair regrowth, or your hair loss willbegin again

Other information

Before use, read all information on this carton
Keep the carton. It contains important information.
Store at 20 to 25℃ (68 to 77°F).
Contents are under pressure. Avoid puncturing orincinerating. Keep away from heat, and storebelow 120°F (49℃).

Inactive ingredients

Water, Alcohol, Biotin, Niacinamide, Panthenol, Jamaican Black Castor Oil, Rosemary Oil, Batana Oil, Ginseng Extract, Ginger Extract, Carthamus Tinctorius L. Extract, Cortex Dictamni, Fructus Ligustri Lucidi Extract, Ligusticum Chuanxiong Hort Extract, Glycyrrhiza Uralensis Fisch Extract, Arctium Lappa L., Angelica Sinensis, Cacumen Platycladi Orientalis P.E., Polygonum Multiflorum Thunb, Capsaicin, Collagen.

Questions

Email at support@giottousa.com